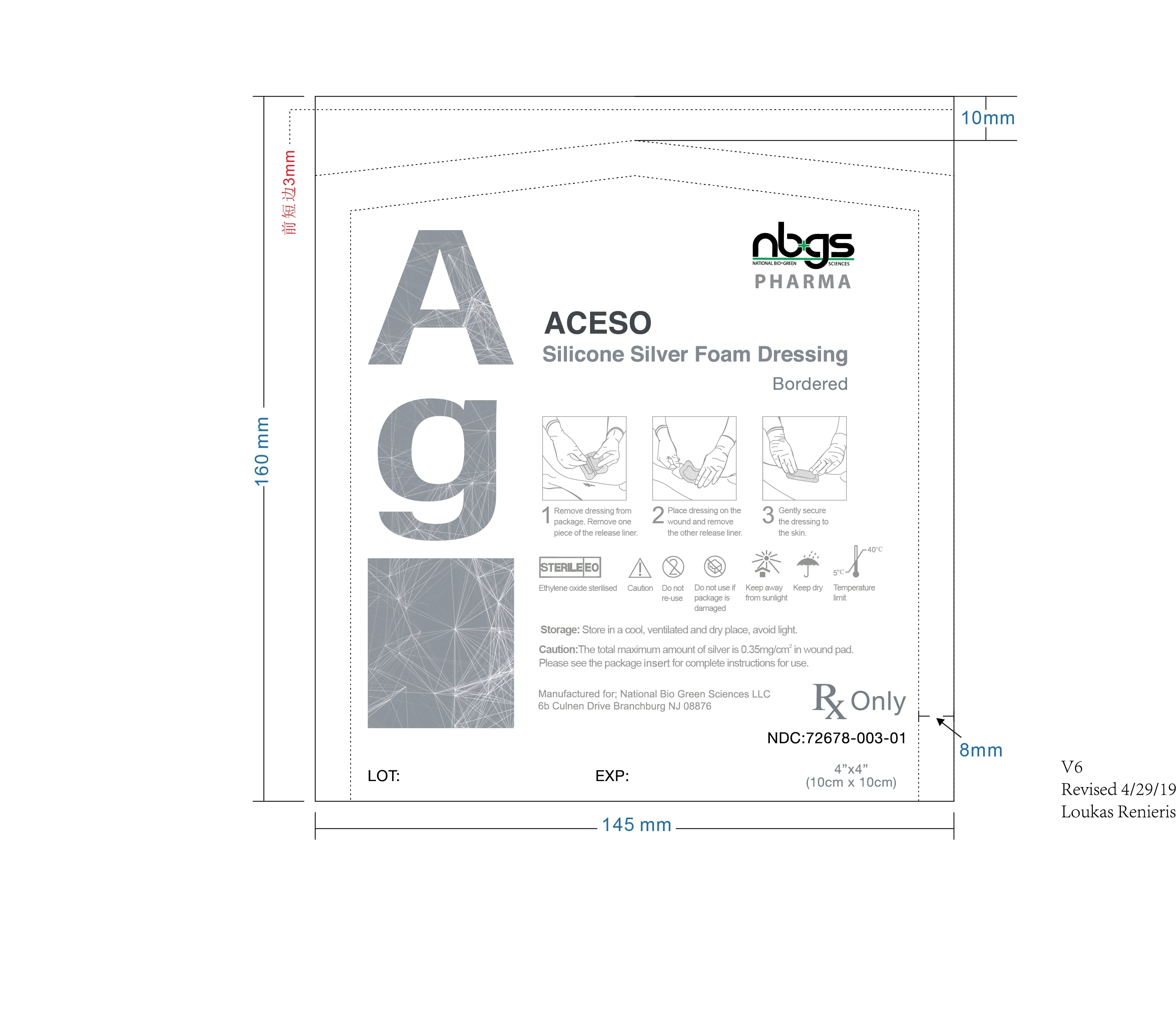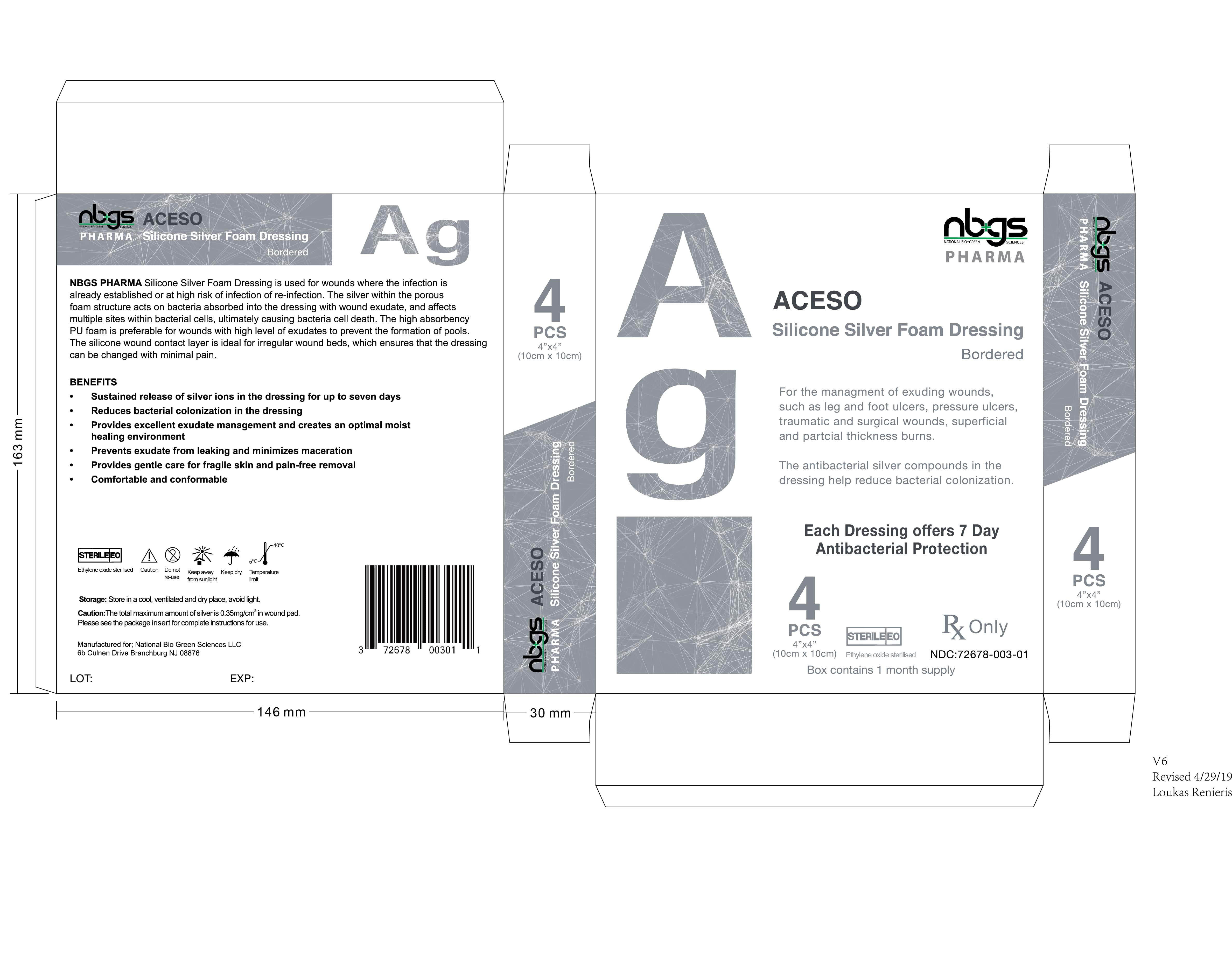 DRUG LABEL: ACESO Ag Silver Silicone Foam Wound Dressing
NDC: 72678-003
Manufacturer: NATIONAL BIO GREEN SCIENCES LIMITED LIABILITY COMPANY
Category: other | Type: MEDICAL DEVICE
Date: 20190821

ACESO Ag, Silver Silicone Foam Wound Dressing

-----------------------------
ACESO Ag, Silicone Silver Foam Dressing, Rx Only ACESO Ag, Silicone Silver Foam Dressing consists of 0.25-0.35mg/cm2 silver ions, and it has been shown that antibacterial effectiveness within the dressing for up to 7 days, as demonstrated in vitro.

Indications

For prescription use only.
ACESO Ag, Silicone Silver Foam Dressing is indicated for the treatment of exuding wounds, such as leg and foot ulcers, pressure ulcers, traumatic and surgical wounds, superficial and partial thickness burns.

DESCRIPTION

ACESO Ag, is an absorbent Silicone Silver Foam Dressing used for the management of exudative wounds. It provides a physiologically favorable moist wound environment for wound healing. ACESO Ag absorbs excess wound exudate. ACESO Ag uses silver as a preservative to control bacterial growth within the foam dressing.

ACESO Ag, Silicone Silver Foam Dressing provides a physiologically favorable environment that encourages wound healing and conforms to the wound site. It is easy to use, biocompatible and biodegradable. ACESO Ag, supports natural autolysis by rehydrating and softening necrotic tissue and eschar thereby encouraging autolytic debridement. The silver preservative in the dressing controls microbial growth for up to 7 days within the dressing, as demonstrated in vitro.

Product Administration

1. Clean the wound with sterile water or normal saline and dry the surrounding skin gently.

2. Remove the release films to cover the wound according to the wound area. The dressing should overlap
the dry surrounding skin by at least 1-2 cm.
3. The frequency of replacing depends on patient's conditions and the exudates situation, such as every 24 hours or longer, but cannot exceed more than 7 days.
Note: Dressing may be moistened with sterile water or normal saline to ease removal.

Warnings

1. ACESO Silicone Ag Foam Dressing is a single use. Do not reuse.
2. ACESO Silicone Ag Foam Dressing is sterile. Do not use it if the pouch is damaged or opened prior to use.
3. Do not suggest using this product on dry wounds.
4. Do not use ACESO Silicone Ag Foam Dressing together with oxidant, such as hypochlorite solutions or hydrogen peroxide.
5. ACESO Silicone Ag Foam Dressing may cause transient discoloration of the wound bed and surrounding skin. Frequent or prolonged use
of this product may result in permanent discoloration of skin.
6. ACESO Silicone Ag Foam Dressing does not replace the need for systemic therapy or other adequate infection treatment in the event of
clinical infection.
7. Do not use ACESO Silicone Ag Foam Dressing during radiation treatment or examinations, such as X-ray, magnetic resonance imaging
[MRI] ultrasound or diathermy.
8. Avoid contact with electrodes or conductive gels during electronic measurements, such as electrocardiograms [ECG], and
electroencephalograms [EEG].
9. ACESO Silicone Ag Foam Dressing is only used for external use.

CONTRAINDICATIONS

Contraindicated for individuals with a known sensitivity to silver and any other contents of the dressing.

PRECAUTIONS

Cautions
Federal law restricts this device to sale by or on the order of a physician. (Rx Only)
The total maximum amount of silver is 0.35mg/cm2 in wound pad.

How Supplied

ACESO Ag, Silver Silicone Foam Wound Dressings are packaged in 4 sterile bandages per pack.

NDC 72678-003-01.

Storage and Disposal

1. Please store the product in cool and dry place, and avoid light.

2. Disposal should be handled according to local environmental procedures.

SHELF LIFE: 3 years from date of manufacture.

Manufactured for:
National Bio Green Sciences LLC, Branchburg, NJ
Questions: National Bio Green Sciences, LLC
Call: 1-908-255-4133 or
Email: info@nbgsusa.com